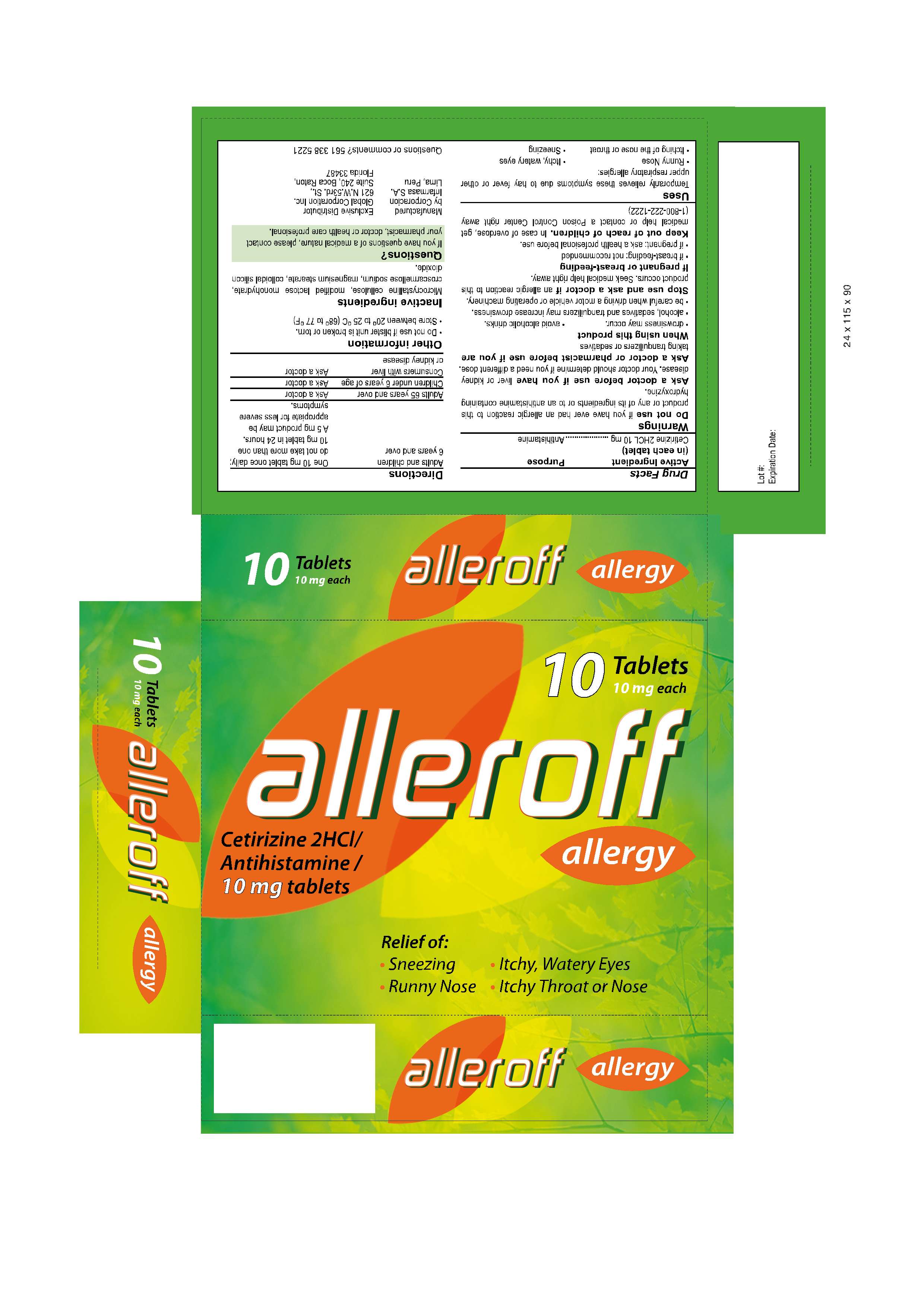 DRUG LABEL: ALLEROFF
NDC: 16853-1305 | Form: TABLET
Manufacturer: Corporacion Infarmasa
Category: otc | Type: HUMAN OTC DRUG LABEL
Date: 20100215

ACTIVE INGREDIENTS: CETIRIZINE HYDROCHLORIDE 10.0 mg/1 1
INACTIVE INGREDIENTS: CELLULOSE, MICROCRYSTALLINE 150.0 mg/1 1; CROSCARMELLOSE SODIUM 5.0 mg/1 1; LACTOSE MONOHYDRATE 50.0 mg/1 1; MAGNESIUM STEARATE 2.0 mg/1 1

Drug Facts

ACTIVE INGREDIENT

Cetirizine HCL 10 mg..........Antihistamine

Ask a doctor before use if you have liver or kidney disease. Your doctor should determine if you need a different dose.

Ask a doctor or pharmacist before use if you are taking tranquilizers or sedatives.
When using this product:

- Drowsiness may occur
- Avoid alcoholic drinks
- Alcohol, sedatives and tranquilizers may increase drowsiness
- Be careful when driving a motor vehicle or operating machinery

Do not use if you have ever had an allergic reaction to this product or any of its ingredients or to an antihistamine containing hidroxyzine

KEEP OUT OF REACH OF CHILDREN

In case of overdose, get medical help or contact a Poison Control Center right away. (1-800-222-1222)

If pregnant or breast feeding:

- if breast feeding: not recommended
- if pregnant: ask a health professional before use

Stop use and ask a doctor if an allergic reaction to this product occurs. Seek medical help right away.

Uses
Temporarily relieves these symptoms due to hay fever or other upper respiratory allergies:

- Runny Nose
- Itchy,water eyes
- Itching of the nose or throat
- Sneezing

QUESTIONS

If you have questions of a medical nature, please contact your pharmacist, doctor or health care profesional

Questions or comments? 561 338 5221

Do not use if blister unit is broken or lorn

Store between 20ºC to 25ºC (68ºF to 77ºF)

DOSAGE AND ADMINISTRATION

Adults and Children 6 years and over One 10 mg tablet once daily;do not take more than one 10 mg tablet in 24 hours. A 5 mg strenght may be appropiate for less severe symptoms

Adults 65 years and over Ask a Doctor

Children under 6 years of age Ask a Doctor

Consumer with liver or kidney disease Ask a Doctor

INACTIVE INGREDIENT

Microcrystalline Cellulose, Lactose Monohydrate, Crosscaramellose Sodium, Magnesium Stearate